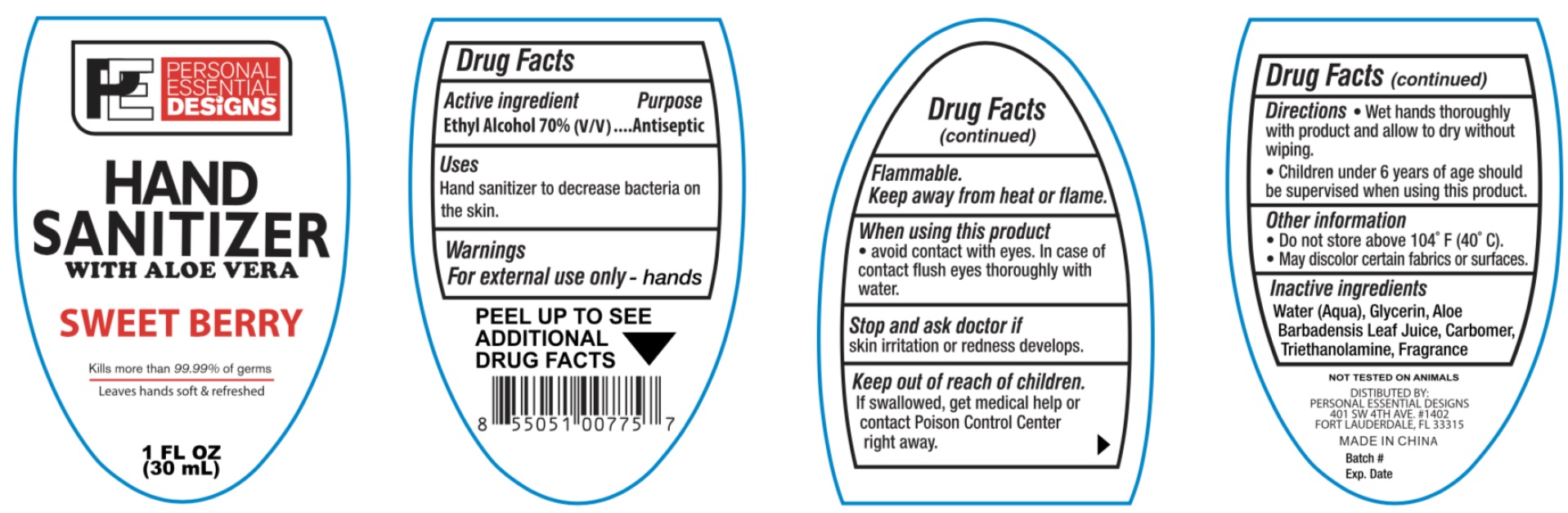 DRUG LABEL: Hand Sanitizer With Aloe Vera Sweet Berry
NDC: 74294-002 | Form: GEL
Manufacturer: Personal Essential Designs, LLC
Category: otc | Type: HUMAN OTC DRUG LABEL
Date: 20200702

ACTIVE INGREDIENTS: ALCOHOL 0.7 mL/1 mL
INACTIVE INGREDIENTS: WATER; GLYCERIN; ALOE VERA LEAF; CARBOMER HOMOPOLYMER, UNSPECIFIED TYPE; TROLAMINE; .ALPHA.-TOCOPHEROL ACETATE

Hand Sanitizer Gel With Aloe Vera Sweet Berry

Active Ingredient

Ethyl Alcohol 70% (V/V)

Purpose

Antiseptic

Uses

Hand sanitizer to decrease bacteria on the skin.

Warnings

For external use only - hands

Flammable. Keep away from heat or flame.

When using this product

avoid contact with eyes. In case of contact flush eyes thoroughly with water.

Stop and ask doctor if

skin irritation or redness develops.

Keep out of reach of children.

If swallowed, get medical help or contact Poison Control Center right away.

Directions

- Wet hands thoroughly with product and allow to dry without wiping.
- Children under 6 years of age should be supervised when using this product.

Other information

- Do not store above 104° F (40° C).
- May discolor certain fabrics or surfaces.

Inactive Ingredients

Water (Aqua), Glycerin, Aloe barbadensis Leaf Juice, Carbomer, Triethanolamine, Fragrance